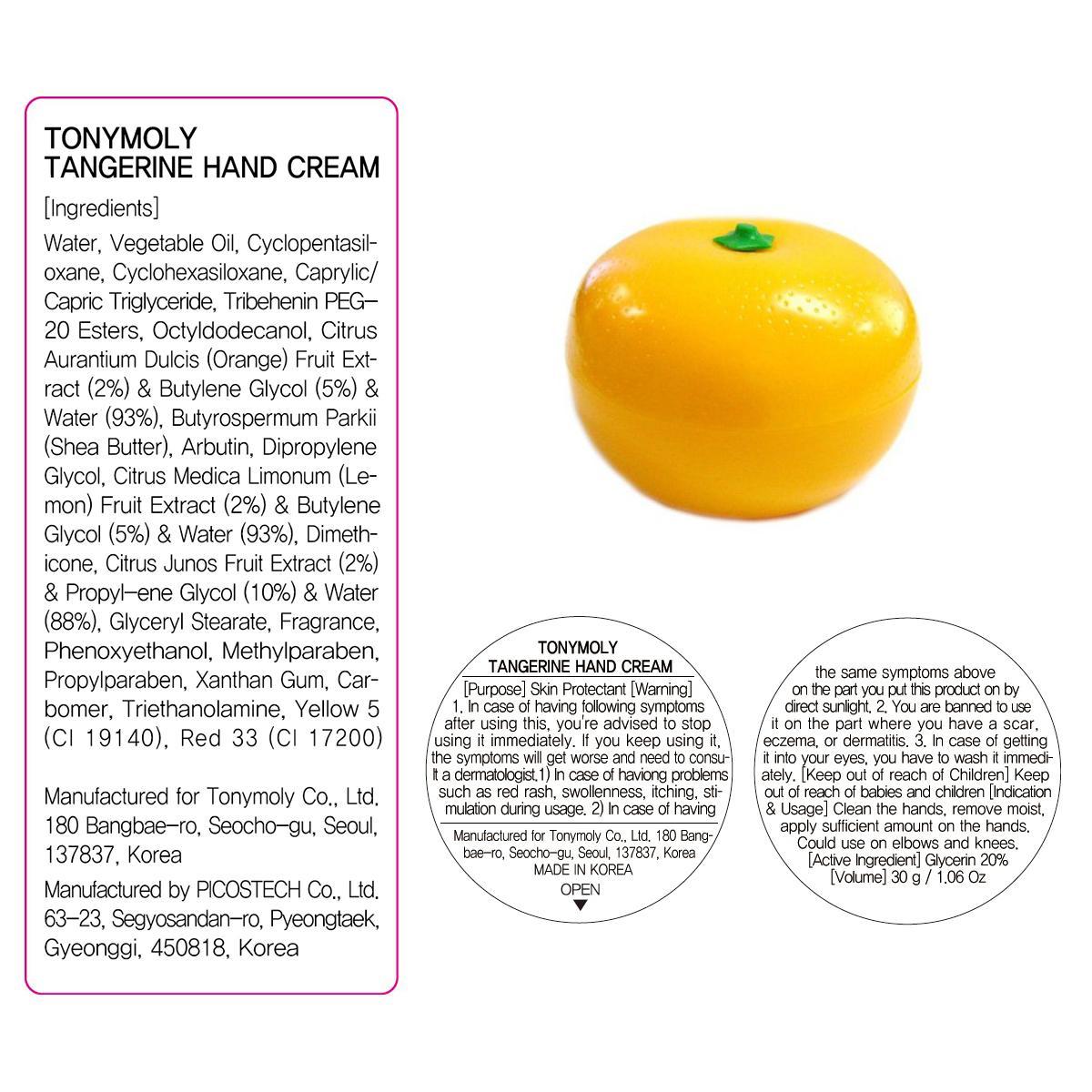 DRUG LABEL: TANGERINE HAND
NDC: 59078-053 | Form: CREAM
Manufacturer: TONYMOLY CO., LTD.
Category: otc | Type: HUMAN OTC DRUG LABEL
Date: 20150306

ACTIVE INGREDIENTS: Glycerin 6 g/30 g
INACTIVE INGREDIENTS: Water; Arbutin

ACTIVE INGREDIENT

Active Ingredient: Glycerin 20%

INACTIVE INGREDIENT

Inactive Ingredients: Water, Vegetable Oil, Cyclopentasiloxane, Cyclohexasiloxane, Caprylic/Capric Triglyceride, Tribehenin PEG-20 Esters, Octyldodecanol, Citrus Aurantium Dulcis (Orange) Fruit Extract (2%)&Butylene Glycol (5%)& Water(93%), Butyrospermum Parkii(Shea Butter), Arbutin, Dipropylene Glycol, Citrus Medica Limonum (Lemon) Fruit Extract(2%) & Butylene Glycol(5%)&Water(93%), Dimethicone, Citrus Junos Fruit Extract(2%)& Propylene Glycol(10%) & Water(88%), Glyceryl Stearate, Fragrance, Phenoxyethanol, Methylparaben, Propylparaben, Xanthan Gum, Carbomer, Triethanolamine, CI 19140, CI 17200

PURPOSE

PURPOSE: Skin Protectant

WARNINGS

Warnings: 1. In case of having following symptoms after using this, you're advised to stop using it immediately. If you keep using it, the symptoms will get worse and need to consult a dermatologist. 1) In case of having problems such as red rash, swollenness, itching, stimulation during usage. 2) In case of having the same symptoms above on the part you put this product on by direct sunlight. 2. You are banned to use it on the part where you have a scar, eczema, or dermatitis. 3. In case of getting it into your eyes, you have to wash it immediately.

Keep out of reach of children: Keep out of reach of babies and children

INDICATIONS & USAGE

INDICATIONS AND USAGE: Clean the hands, remove moist, apply sufficient amount on the hands. Could use on elbows and knees.

DOSAGE & ADMINISTRATION

DOSAGE AND ADMINISTRATION: Take an adequate amount of this product.

PACKAGE LABEL.PRINCIPAL DISPLAY PANEL

Image of carton